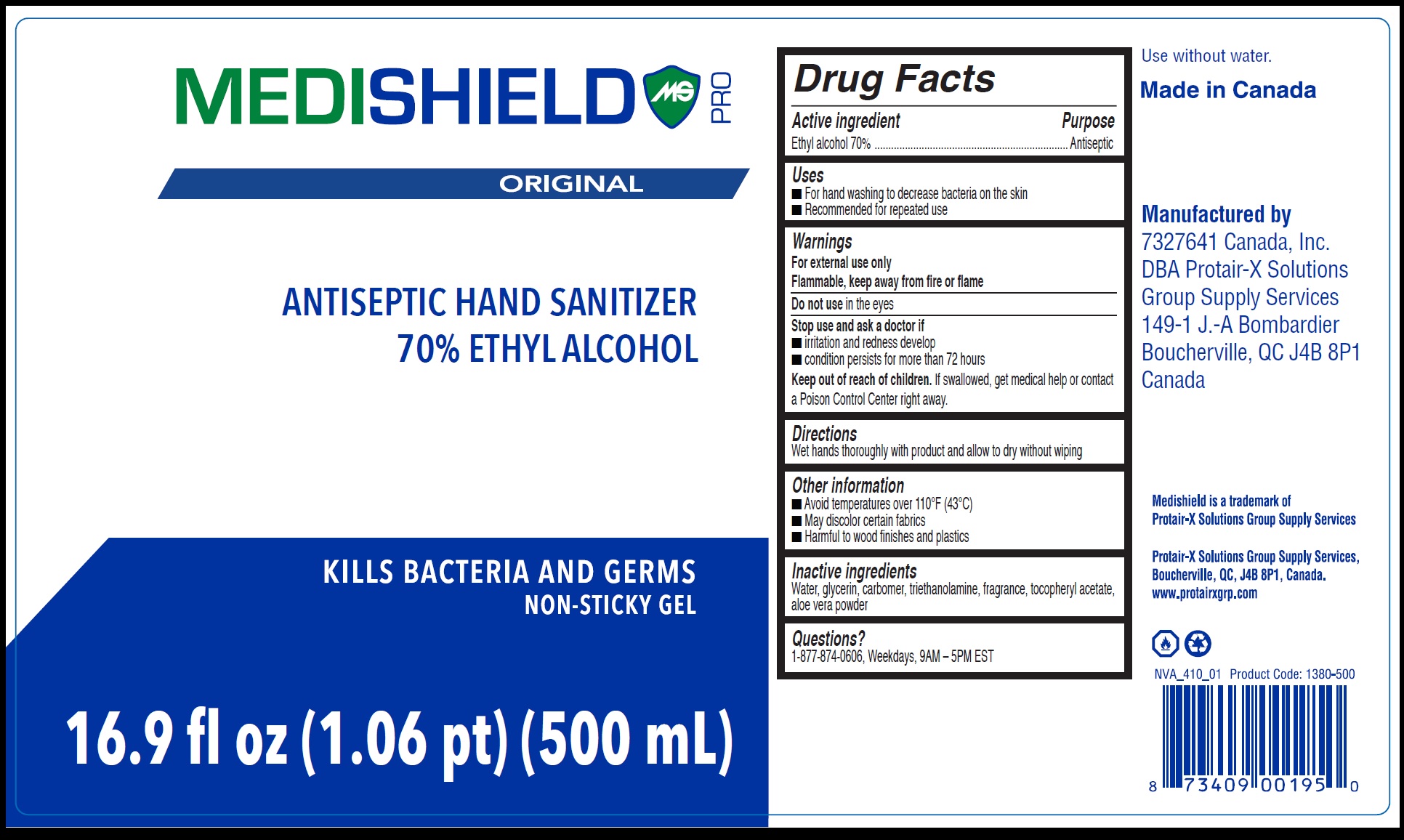 DRUG LABEL: MediShield Pro Original Antiseptic Hand Sanitizer
NDC: 81818-001 | Form: GEL
Manufacturer: 7327641 Canada, Inc.
Category: otc | Type: HUMAN OTC DRUG LABEL
Date: 20210422

ACTIVE INGREDIENTS: ALCOHOL 70 mL/100 mL
INACTIVE INGREDIENTS: WATER; GLYCERIN; CARBOMER HOMOPOLYMER, UNSPECIFIED TYPE; TROLAMINE; .ALPHA.-TOCOPHEROL ACETATE; ALOE VERA LEAF

MediShield Pro Original Antiseptic Hand Sanitizer

Active ingredient

Ethyl alcohol 70%

Purpose

Antiseptic

Uses

- For hand washing to decrease bacteria on the skin
- Recommended for repeated use

Warnings

For external use only
Flammable, keep away from fire or flame

Do not use

in the eyes

Stop use and ask a doctor if

- irritation and redness develop
- condition persists for more than 72 hours

Keep out of reach of children.

If swallowed, get medical help or contact a Poison Control Center right away.

Directions

Wet hands thoroughly with product and allow to dry without wiping

Other information

- Avoid temperatures over 110°F (43°C)
- May discolor certain fabrics
- Harmful to wood finishes and plastics

Inactive ingredients

Water, glycerin, carbomer, triethanolamine, fragrance, tocopheryl acetate, aloe vera powder

Questions?

1-877-874-0606, Weekdays, 9AM – 5PM EST